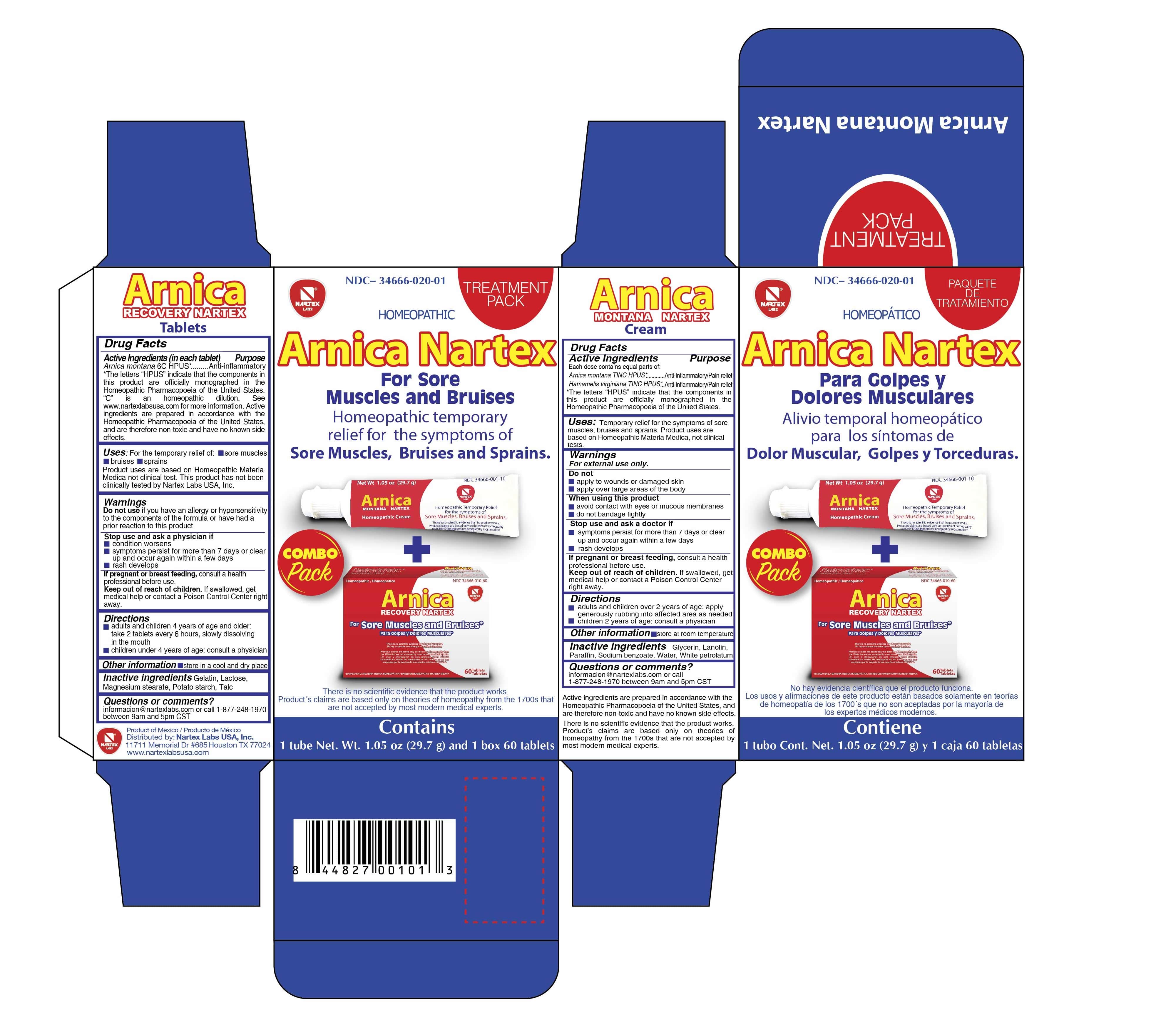 DRUG LABEL: Arnica Treatment Pack
NDC: 34666-020 | Form: KIT | Route: ORAL
Manufacturer: Nartex Laboratorios Homeopaticos SA DE CV
Category: homeopathic | Type: HUMAN OTC DRUG LABEL
Date: 20190411

ACTIVE INGREDIENTS: ARNICA MONTANA 6 [hp_C]/1 1; ARNICA MONTANA 1 [hp_X]/1 g; HAMAMELIS VIRGINIANA LEAF 1 [hp_X]/1 g
INACTIVE INGREDIENTS: LACTOSE, UNSPECIFIED FORM; STARCH, POTATO; TALC; GELATIN; MAGNESIUM STEARATE; WATER; PETROLATUM; GLYCERIN; PARAFFIN; SODIUM BENZOATE; LANOLIN

Active Ingredient (in each tablet)

Arnica Montana 6C HPUS*

*The letters "HPUS" indicate that the components in this product are officially monographed in the Homeopathic Pharmacopoeia of the United States. "C" is an homeopathic dilution. See www.nartexlabsusa.com formore information. Active ingredients are prepared in accordance with the Homeopathic Pharmacopoeia of the United States, and are therefore non-toxic and have no known side effects.

Purpose

Arnica Montana 6C HPUS* .....Anti-inflammatory

Uses

For the temporary relief of sore muscles, bruises, sprains

Product uses are based on Homeopathic Materia Medica not clinical tests. This product has not been clinically tested by Nartex Labs USA, Inc.

Warnings

Do not use if you have an allergy or hypersensitivity to the components of the fourmal or have had a prior reaction to this product.

Stop use and ask a physcian if

- condition worsens
- symptoms persist for more than 7 days or clear up and occur again within a few days
- rash develops.

PREGNANCY OR BREAST FEEDING

If pregnant or breastfeeding, consult a health professional before use.

Keep out of reach of children. If swallowed, get medical help or contact a Poison Control Center right away.

Directions

- Adults and children 4 yers of age and older: take 2 tablets every 6 hours, slowly dissolving in the mouth
- Children under 4 years of age: consult a physician

Other Information

Store in a cool and dry place.

Inactive Ingredients

Gelatin, Lactose, Magnesium stearate, Potato stach, Talc

Questions or Comments?

Informacion@nartexlabs.com or call 1-877-248-1970 between 9am and 5pm CST.

Product of Mexico / Producto de Mexico

Distributed by: Nartex Labs, USA, Inc.

11711 Memorial Drive #685 Houston, TX 77024

www.nartexlabsusa.com

Active Ingredients

Each does contains equial parts of:

Anrica Montana TINC HPUS*

Hamamelis virginiana TINC HPUS*

Purpose

Arnica Montana TINC HPUS*.......Anti-inflammatory/Pain Relief

Hamamelis virginiana TINC HPUS.....Anti-inflammatory/Pain Relief

Uses

Temporary relief for the symptoms of sore muscles, bruises, and sprains. Product uses are based on Homeopathic Materia Medica not clinical tests.

Warnings

For external use only.

Do not

- Apply to wounds tor damaged skin
- apply over large areas of the body

When using this product

- avoid contact with eyes or mucous membranes
- do not bandage tightly

Stop use and ask a doctor if

- symptoms persist for more than 7 das or clear up and occur again within a few days
- rash develops

PREGNANCY OR BREAST FEEDING

If pregnant or breast feeding, consult a health professional before use,

Keep out of reach of children. If swallowed, get medical help or contact a Poison Control Center right away.

Directions

- Adults and children over 2 years of age: apply generously rubbing into affected area as needed
- children 2 years of age: consult a physcian

Other Information

Store at room temperature

Inactive Ingredients

Glycerin, Lanolin, Paraffin, Sodium benzoate, Water, White petrolatum

Questions or Comments?

informacion@nartexlabs.com or call 1-877-248-1970 between 9am and 5pm CST.

Active Ingredients are prepared in accordance with the Homeopathic Pharmaocopoeia of the United States, and are therefore non-toxic and have no known side effects.

There is no scientific evidence that the product works. Product's claims are baed only on theories of homeopathy from the 1700's that are not accepted by most modern medical experts.

Principal Display Panel

HOMEOPATHIC

Arnica Nartex

for sore muscles and bruises

Homeopathic temporary relief for the symptoms of sore muscles, bruises, and sprains.

COMBO PACK

There is no scientific evidence that the product works. Product's claims are based only on theories of homeopathy from the 1700's that are not accepted by most modern medical experts.

Contains

1 tube Net. Wt. 1.05oz (29.7g) and 1 Box 60 tablets